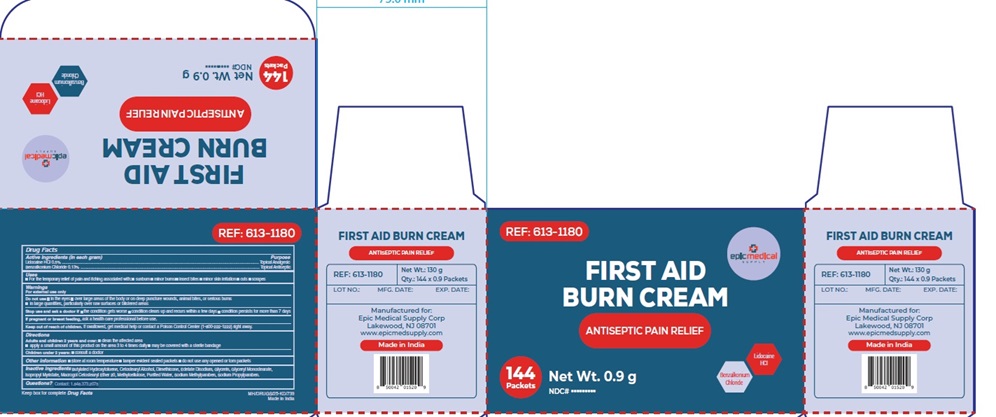 DRUG LABEL: FIRST AID BURN
NDC: 82749-009 | Form: CREAM
Manufacturer: Epic Medical Supply Corp
Category: otc | Type: HUMAN OTC DRUG LABEL
Date: 20240604

ACTIVE INGREDIENTS: LIDOCAINE HYDROCHLORIDE 5 mg/1 g; BENZALKONIUM CHLORIDE 1.3 mg/1 g
INACTIVE INGREDIENTS: BUTYLATED HYDROXYTOLUENE; CETOSTEARYL ALCOHOL; DIMETHICONE; EDETATE DISODIUM; GLYCERIN; GLYCERYL MONOSTEARATE; ISOPROPYL MYRISTATE; POLYOXYL 20 CETOSTEARYL ETHER; METHYLCELLULOSE, UNSPECIFIED; WATER; METHYLPARABEN SODIUM; PROPYLPARABEN SODIUM

Active Ingredients

Lidocaine HCL 0.5% Topical Analgesic

Benzalkonium Chloride 0.13% Topical Antiseptic

Purpose

Topical Analgesic

Topical Antiseptic

Uses

For temporary relief of pain and itching associated with:

- Sunburn
- Minor burns,
- Insect bites,
- Minor skin irritation,
- Cuts
- Scrapes

Warnings

For external use only

Do not use

- in the eyes
- over large areas of the body or on deep puncture wounds, animal bites, or serious burns
- in large quantities, particularly over raw surfaces or blistered areas

Stop use and ask a doctor if

- the condition gets worse
- condition clears up and recurs within a few days
- condition persists for more than 7 days

- If pregnant or breast feeding, ask a health care professional before use.
- Keep out of reach of children. If swallowed, get medical help or contact a Poison Control Center (1-800-222-1222) right away.

Directions

- Adults and children 2 years and over: clean the affected area apply a small amount of this product on the area 3 to 4 times daily may be covered with a sterile bandage
- Children under 2 years: consult a doctor

Other information

- Store at room temperature
- tamper evident sealed packets
- do not use any opened or torn packets

Inactive ingredients

Butylated Hydroxytoluene, Cetostearyl Alcohol, Dimethicone, Edetate Disodium, Glycerin, Glyceryl Monostearate, Isopropyl Myristate, Macrogol Cetostearyl Ether 20, Methylcellulose, Purified Water, Sodium Methylparaben, Sodium Propylparaben.

Questions?

Contact: 1.848.373.2075